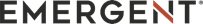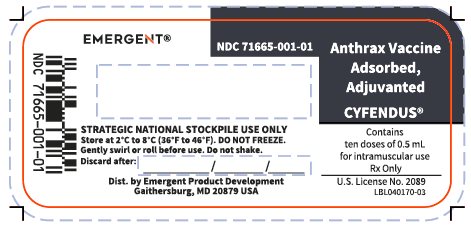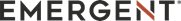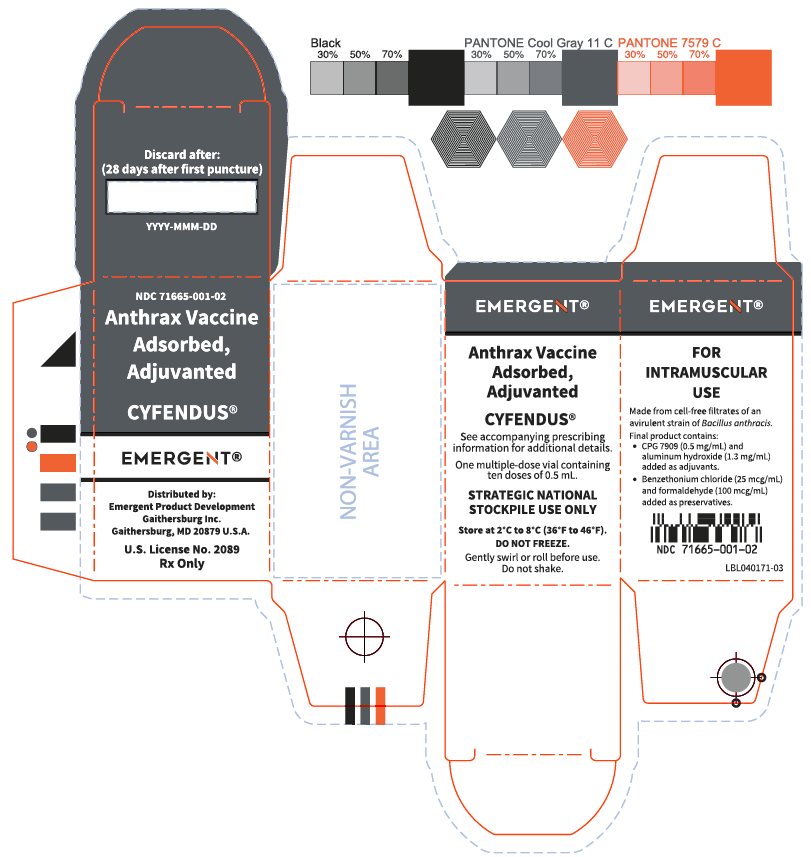 DRUG LABEL: CYFENDUS
NDC: 71665-001 | Form: INJECTION, SUSPENSION
Manufacturer: Emergent Product Development Gaithersburg Inc.
Category: other | Type: VACCINE LABEL
Date: 20260225

ACTIVE INGREDIENTS: BACILLUS ANTHRACIS STRAIN V770-NP1-R ANTIGENS 100 ug/1 mL
INACTIVE INGREDIENTS: AGATOLIMOD SODIUM 0.5 mg/1 mL; ALUMINUM HYDROXIDE 1.3 mg/1 mL; BENZETHONIUM CHLORIDE 25 ug/1 mL; FORMALDEHYDE 100 ug/1 mL; SODIUM CHLORIDE 8.5 mg/1 mL; WATER

HIGHLIGHTS OF PRESCRIBING INFORMATION

These highlights do not include all the information needed to use CYFENDUS safely and effectively. See full prescribing information for CYFENDUS.
CYFENDUS® (Anthrax Vaccine Adsorbed, Adjuvanted) injectable suspension, for intramuscular use
Initial U.S. Approval: 2023

1 INDICATIONS AND USAGE

CYFENDUS (Anthrax Vaccine Adsorbed, Adjuvanted) is a vaccine indicated for post-exposure prophylaxis of disease following suspected or confirmed exposure to Bacillus anthracis in persons 18 through 65 years of age when administered in conjunction with recommended antibacterial drugs.
The efficacy of CYFENDUS for post-exposure prophylaxis is based solely on studies in animal models of inhalational anthrax. (1)

2 DOSAGE AND ADMINISTRATION

For intramuscular use.

Administer two doses (0.5 mL each) intramuscularly two weeks apart. (2.1, 2.2)

3 DOSAGE FORMS AND STRENGTHS

Injectable suspension; each dose is 0.5 mL. (3)

4 CONTRAINDICATIONS

Severe allergic reaction (e.g., anaphylaxis) after a previous dose of CYFENDUS, BioThrax® or to any component of the vaccine. (4, 11)

5 WARNINGS AND PRECAUTIONS

Appropriate medical treatment must be available to manage possible anaphylactic reactions following administration of CYFENDUS. (5.1)
CYFENDUS can cause fetal harm when administered to a pregnant individual. In an observational study, there were more birth defects in infants born to individuals vaccinated with BioThrax (a licensed anthrax vaccine with the same active ingredient as CYFENDUS) in the first trimester compared with infants born to individuals vaccinated post pregnancy or individuals never vaccinated with BioThrax. (5.3)

6 ADVERSE REACTIONS

The most common (≥10%) injection-site adverse reactions reported were tenderness (88.1%), pain (86.3%), arm motion limitation (63.7%), warmth (51.2%), induration (37.5%), itching (21.9%), swelling (19.7%), and erythema/redness (17.9%). The most common systemic adverse reactions (≥10%) were muscle aches (75.2%), tiredness (67.1%) and headache (58.0%). (6)

To report SUSPECTED ADVERSE REACTIONS, contact Emergent BioSolutions at 1-800-768-2304 or medicalinformation@ebsi.com or VAERS at 1-800-822-7967 or www.vaers.hhs.gov.

FULL PRESCRIBING INFORMATION

1 INDICATIONS AND USAGE

CYFENDUS (Anthrax Vaccine Adsorbed, Adjuvanted) is a vaccine indicated for post-exposure prophylaxis of disease following suspected or confirmed exposure to Bacillus anthracis in persons 18 through 65 years of age when administered in conjunction with recommended antibacterial drugs.

The efficacy of CYFENDUS for post-exposure prophylaxis (PEP) is based solely on studies in animal models of inhalational anthrax.

2 DOSAGE AND ADMINISTRATION

For intramuscular use.

2.1 Dose and Schedule

Administer CYFENDUS by intramuscular injection as a series of two doses (0.5 mL each) two weeks apart (at Week 0 and 2) post-exposure combined with antibacterial therapy.

2.2 Administration

Gently swirl or roll the vial to ensure that the vaccine is a homogeneous milky-white suspension. To avoid foaming DO NOT shake.

Parenteral drug products should be inspected visually for particulate matter and discoloration prior to administration, whenever solution and container permit. If either of these conditions exist, do not administer the vaccine and discard the vial. Once the stopper of the multiple-dose vial has been pierced, discard the vial within 28 days [see How Supplied/Storage and Handling (16)].

Administer CYFENDUS intramuscularly.

3 DOSAGE FORMS AND STRENGTHS

CYFENDUS is an injectable suspension. Each dose is 0.5 mL.

4 CONTRAINDICATIONS

Do not administer CYFENDUS to individuals with a history of a severe allergic reaction (e.g., anaphylaxis) following a previous dose of CYFENDUS, BioThrax or any component of the vaccine [see Description (11)].

5 WARNINGS AND PRECAUTIONS

5.1 Management of Acute Allergic Reactions

Appropriate medical treatment must be available to manage possible anaphylactic reactions following administration of CYFENDUS.

5.2 Altered Immunocompetence

Immunocompromised persons, including those receiving immunosuppressive therapy, may have a diminished immune response to CYFENDUS.

5.3 Pregnancy

CYFENDUS can cause fetal harm when administered to a pregnant individual. In an observational study, there were more birth defects in infants born to individuals vaccinated with BioThrax (a licensed anthrax vaccine with the same active ingredient as CYFENDUS; BioThrax does not contain CPG 7909 adjuvant) in the first trimester compared with infants born to individuals vaccinated post pregnancy or individuals never vaccinated with BioThrax. [see Use in Specific Populations (8.1)]

If CYFENDUS is administered during pregnancy, the vaccinated individual should be apprised of the potential hazard to a fetus.

6 ADVERSE REACTIONS

The most common (≥10%) injection-site adverse reactions reported were tenderness (88.1%), pain (86.3%), arm motion limitation (63.7%), warmth (51.2%), induration (37.5%), itching (21.9%), swelling (19.7%), and erythema/redness (17.9%.). The most common systemic adverse reactions (≥10%) were muscle aches (75.2%), tiredness (67.1%), and headache (58.0%) (see Table 1).

6.1 Clinical Trials Experience

Because clinical trials are conducted under widely varying conditions, adverse reaction rates observed in the clinical trials of a vaccine cannot be directly compared to rates in the clinical trials of another vaccine and may not reflect the rates observed in clinical practice.

The safety of CYFENDUS was evaluated in 4 clinical studies, in which a total of 3,276 participants 18 through 65 years of age received at least one dose of CYFENDUS and were included in a pooled safety population.

Study 1 (NCT01263691) evaluated the safety and immunogenicity of different vaccine formulations administered intramuscularly two weeks apart in participants between 18 and 50 years of age. Seventeen participants received at least one 0.5 mL dose of CYFENDUS.

Study 2 (NCT01770743) evaluated the safety and immunogenicity of different dosing regimens of CYFENDUS in participants between 18 and 50 years of age. Forty-four participants received two doses of CYFENDUS via the intramuscular route two weeks apart.

Study 3 (NCT04067011) investigated potential interactions of intramuscularly administered CYFENDUS with the antibacterials ciprofloxacin or doxycycline, when administered concomitantly in participants between 18 and 45 years of age. Sixty-four participants received only CYFENDUS in the control arm.

Study 4 (NCT03877926) evaluated the safety and immunogenicity of CYFENDUS in participants between 18 and 65 years of age. CYFENDUS was administered intramuscularly as two doses at Weeks 0 and 2, with saline placebo given at Week 4. BioThrax was administered subcutaneously as three doses at Weeks 0, 2, and 4. The number of participants receiving at least one dose of CYFENDUS was 3151, while 2898 participants received the complete two dose regimen. [see Clinical Studies (14.1)]

The mean age for the pooled safety population across Studies 1-4 was 39 years; 32.1% of participants (n=1050) were between 18-30 years of age, 44.2% (n=1447) were between 31 to 50 years of age, and 23.8% (n=779) were between 51-65 years of age. Females comprised 57.8% (n=1895) of the population, with 40.4% (n=1325) being women of childbearing potential. The race distribution was as follows: 77.9% White, 17.1% Black or African American, 1.8% Asian, 1.7% Multiracial, 0.4% American Indian or Alaskan Native, 0.3% Native Hawaiian or Other Pacific Islander, 0.5% Other, and 0.2% Unknown. Most participants (83.9%) were not Hispanic or Latino.

Study 4 Solicited Local and Systemic Adverse Reactions

In Study 4, an active-controlled study, the licensed anthrax vaccine, BioThrax (Anthrax Vaccine Adsorbed), was used as the comparator. Solicited local and systemic adverse reactions reported following administration of any dose of CYFENDUS or BioThrax are presented in Table 1. CYFENDUS was administered intramuscularly as two doses at Weeks 0 and 2, with saline placebo given at Week 4. BioThrax was administered subcutaneously as three doses at Weeks 0, 2, and 4. The number of participants receiving at least one dose of CYFENDUS was 3151, while 2898 participants received the complete two dose regimen of CYFENDUS. There was no notable difference in the frequency of solicited local or systemic adverse reactions after the first or second dose of CYFENDUS, with the exception of itching (10.3% after first CYFENDUS dose vs. 16.8% after second dose), erythema/redness (7.4% after first CYFENDUS dose vs. 14.8% after second dose), swelling (10.2% after first CYFENDUS dose vs. 15.9% after second dose) and fever (2.7% after first CYFENDUS dose vs. 5.0% after second dose).

Table 1 Percentage (%) of Participants with Solicited Local or Systemic Adverse Reactions within 7 Days Following Administration of Any Vaccine Dosea in Study 4b
 | CYFENDUS | CYFENDUS | CYFENDUS | BioThrax | BioThrax | BioThrax
 | N | Any Grade | Grade 3+ | N | Any Grade | Grade 3+
Local Adverse Reactionsc
Any Injection Site Reaction | 3106 | 93.0% | 3.8% | 527 | 94.9% | 4.6%
Tenderness | 3106 | 88.1% | 1.7% | 527 | 89.9% | 0.8%
Paind | 3106 | 86.3% | 2.1% | 527 | 87.9% | 0.9%
Arm Motion Limitation | 3106 | 63.7% | 1.7% | 527 | 51.4% | 0.4%
Warmth | 3106 | 51.2% | 0.7% | 527 | 68.7% | 0.2%
Induratione | 3106 | 37.5% | 0.3% | 527 | 75.5% | 1.1%
Itching | 3106 | 21.9% | 0.4% | 527 | 58.8% | 0.8%
Swellinge | 3106 | 19.7% | 0.4% | 527 | 55.4% | 1.3%
Erythema/ Rednessf | 3106 | 17.9% | 0.9% | 527 | 53.9% | 1.9%
Bruising | 3106 | 17.2% | 0.3% | 527 | 34.9% | 0.0%
Systemic Adverse Reactionsg
Any Systemic Reaction | 3115 | 84.3% | 6.6% | 528 | 78.4% | 3.8%
Muscle Ache | 3106 | 75.2% | 3.5% | 527 | 63.4% | 1.9%
Tiredness | 3106 | 67.1% | 2.9% | 527 | 53.7% | 1.7%
Headache | 3106 | 58.0% | 3.2% | 527 | 47.6% | 2.1%
Feverh | 3113 | 6.8% | 0.7% | 527 | 1.7% | 0.4%
a 3151 participants received at least one dose, and 2898 participants received two doses of CYFENDUS.
b Percentage of participants reporting solicited local or systemic adverse reactions in e-diaries and during in-clinic reactogenicity assessments for at least 7 days following any dose (CYFENDUS up to two doses intramuscularly, BioThrax up to three doses subcutaneously).
c No Grade 4 local adverse reactions were reported for CYFENDUS. For all local adverse reactions, Grade 3 included a criterion that the symptom prevents activities of daily living or requires treatment. Some local adverse reactions included additional or alternative Grade 3 criteria as noted in the respective footnotes.
d Pain: Grade 3 = Pain requires use of narcotic pain reliever or prevents daily activity; Grade 4 = Emergency Room visit or hospitalization.
e Induration/swelling: Any Grade = ≥2.5 cm and does not interfere with activity; Grade 3 = >10 cm or prevents daily activity; Grade 4 = Necrosis.
f Erythema/redness: Any Grade = ≥2.5 cm; Grade 3 = >10 cm; Grade 4 = Necrosis or exfoliative dermatitis.
g No Grade 4 systemic adverse reactions were reported for CYFENDUS. Systemic adverse event: Grade 1 = Mild; Grade 2 = Moderate; Grade 3 = Severe (symptom prevents activities of daily living or requires treatment); Grade 4 = Severe (potentially life threatening).
h Fever (oral temperature): Grade 1 = 38.0-38.4°C; Grade 2 = 38.5-38.9°C; Grade 3 = 39.0-40°C; Grade 4 = >40°C.

Serious Adverse Events (SAEs) and Deaths

In the pooled safety population, serious adverse events including deaths were monitored for up to one year following the last vaccination. None of the reported deaths (n=6, 0.2%) or SAEs (n=62, 1.9%) were determined to be related to the administration of CYFENDUS.

Potentially Immune-mediated Adverse Events

In the pooled safety population, participants were monitored for the occurrence of new-onset potentially immune-mediated adverse events for 12 months after the first dose of vaccine. Events were adjudicated as to whether they were of autoimmune etiology by an external expert blinded to treatment assignment. As determined by the adjudicator, three events of autoimmune etiology in three participants were considered possibly related to the administration of CYFENDUS: (1) a case of ulcerative colitis that occurred 208 days after the administration of CYFENDUS, (2) a case of chronic idiopathic urticaria that occurred 76 days after the administration of CYFENDUS and (3) a case of diffuse alopecia that occurred 17 days after the administration of CYFENDUS.

6.2 Postmarketing Experience

There is no postmarketing experience following administration of CYFENDUS. However, the postmarketing safety experience with BioThrax is relevant because BioThrax and CYFENDUS contain the same active ingredient and are manufactured similarly. BioThrax does not contain CPG 7909 adjuvant.

The following adverse events have been spontaneously reported during the postmarketing use of BioThrax and may occur in people receiving CYFENDUS. Because these events are reported voluntarily from a population of uncertain size, it is not always possible to reliably estimate their frequency or establish a causal relationship to vaccine exposure. Adverse events included below are listed due to one or more of the following factors: (1) seriousness of the event, (2) number of reports, or (3) strength of causal relationship to BioThrax.

- Blood and lymphatic system disorders: Lymphadenopathy
- Gastrointestinal disorders: Nausea
- Immune system disorders: Allergic reactions (including anaphylaxis, angioedema, rash, urticaria, pruritus, erythema multiforme, anaphylactoid reaction, and Stevens-Johnson syndrome)
- Nervous system disorders: Paresthesia, syncope, dizziness, tremor, ulnar nerve neuropathy
- Musculoskeletal, connective tissue, and bone disorders: Arthralgia, arthropathy, myalgia, rhabdomyolysis, alopecia
- General disorders and administration site conditions: Malaise, pain, cellulitis, flu-like symptoms
- Psychiatric disorders: Insomnia
- Skin and subcutaneous tissue disorders: Pruritus, rash, urticaria
- Vascular disorders: Flushing

Reports of the following were also received: multisystem disorder defined as chronic symptoms involving at least two of the following three categories: fatigue, mood-cognition, and musculoskeletal system.

8 USE IN SPECIFIC POPULATIONS

8.1 Pregnancy

Risk Summary

All pregnancies have a risk of birth defect, loss, or other adverse outcomes. In clinically recognized pregnancies in the US general population, the estimated background risk of major birth defects is 2% to 4% and of miscarriage is 15% to 20%.

There are no adequate and well-controlled studies of CYFENDUS in pregnant individuals.

Available human data on CYFENDUS administered to pregnant individuals do not establish the presence or absence of vaccine-associated risks in pregnancy (see Human Data). However, available data on BioThrax (a licensed anthrax vaccine), administered to pregnant individuals are relevant to CYFENDUS because BioThrax and CYFENDUS contain the same active ingredient and are manufactured similarly. BioThrax does not contain CPG 7909 adjuvant. Data are available from a BioThrax observational study and pregnancy exposure registry.

In the observational study there were more birth defects in infants born to individuals vaccinated with BioThrax in the first trimester compared with individuals vaccinated post pregnancy or individuals never vaccinated with BioThrax. Data from the BioThrax pregnancy exposure registry do not establish the presence or absence of vaccine-associated risks in pregnancy (see Human Data).

In a developmental study with an embryo-fetal development toxicity phase, female rats were administered a full human dose (0.5 mL) of CYFENDUS twice prior to mating and once during gestation. This study revealed no evidence of harm to the fetus, changes in reproductive performance, or adverse effects on post-natal development due to the vaccine (see Animal Data).

Data

Human Data

In pre-licensure clinical studies of CYFENDUS, women underwent pregnancy testing immediately prior to administration of each dose of CYFENDUS. Despite this pregnancy screening regimen, some subjects were vaccinated with CYFENDUS very early in pregnancy before human chorionic gonadotropin was detectable (n=10) or in the 30 days prior to pregnancy onset (n=1). Of the 11 pregnancies (one twin pregnancy), 1 (9.1%) resulted in miscarriage and there were 2 infants (18.2%) born with major birth defects.

An observational study examined the rate of birth defects among 37,140 infants born to US military service personnel who received BioThrax prior to, during, and post pregnancy between 1998 and 2004. In this study, birth defects were slightly more common in first trimester-exposed infants (4.68%) when compared with infants of individuals vaccinated post pregnancy (3.85%) (odds ratio = 1.20; 95% confidence interval: 1.005, 1.43) or when compared with individuals never vaccinated with BioThrax (4.03%) (odds ratio = 1.20; 95% confidence interval: 1.02, 1.42)^1.

A pregnancy exposure registry was conducted in individuals who received BioThrax. Of 91 individuals who reported pregnancy outcomes, the majority of exposures were in the first trimester (n=89), and there were two infants with major birth defects (2.2%) and no miscarriages.

Animal Data

In a pre- and post-natal developmental study with an embryo-fetal development toxicity phase performed in female rats, a full human dose (0.5 mL) of CYFENDUS was administered by intramuscular injection on three occasions: 14 days prior to start of cohabitation, on the day of cohabitation, and on Gestation Day 7. No vaccine-related adverse effects on fetal development, reproductive performance, or pre- and post-natal development up to post-natal day 21 in the offspring were reported.

8.2 Lactation

Risk Summary

It is not known whether CYFENDUS is excreted in human milk. Human data are not available to assess the impact of the vaccine on milk production, its presence in breast milk, or its effects on the breastfed child. The developmental and health benefits of breastfeeding should be considered along with the mother's clinical need for CYFENDUS and any potential adverse effects on the breastfed child, or from the underlying maternal condition. For preventive vaccines, the underlying maternal condition is susceptibility to disease prevented by the vaccine.

8.4 Pediatric Use

Safety and effectiveness of CYFENDUS in individuals younger than 18 years of age have not been established.

8.5 Geriatric Use

Safety and effectiveness of CYFENDUS in individuals older than 65 years of age have not been established.

11 DESCRIPTION

CYFENDUS (Anthrax Vaccine Adsorbed, Adjuvanted) is a sterile, milky-white injectable suspension for intramuscular use.

CYFENDUS is made from cell-free filtrates of microaerophilic cultures of an avirulent, nonencapsulated strain of B. anthracis. The production cultures are grown in a chemically defined protein-free medium consisting of a mixture of amino acids, vitamins, inorganic salts, and sugars. CYFENDUS is prepared from sterile culture filtrates containing proteins released during growth, including the 83-kDa protective antigen protein, and contains no dead or live bacteria. The sterile culture filtrates containing the proteins are adsorbed onto aluminum hydroxide adjuvant and combined with a saline preservative solution containing the excipients sodium chloride, formaldehyde, benzethonium chloride, and water for injection. CPG 7909 adjuvant is added to the preservative solution containing the adsorbed proteins to form CYFENDUS.

CPG 7909 adjuvant is a synthetic DNA molecule 24 nucleotides in length with a nuclease-resistant phosphorothioate backbone.

CYFENDUS contains 100 mcg/mL total adsorbed cell-free filtrate, 1.3 mg/mL aluminum adjuvant, 0.5 mg/mL CPG 7909 adjuvant, and 0.85% sodium chloride, with 25 mcg/mL benzethonium chloride and 100 mcg/mL formaldehyde added as preservatives. A single dose of CYFENDUS is 0.5 mL.

12 CLINICAL PHARMACOLOGY

12.1 Mechanism of Action

Anthrax is an infectious disease caused by the Gram-positive, spore-forming bacterium B. anthracis.

CYFENDUS induces antibodies against protective antigen protein that may contribute to protection by neutralizing the activities of the cytotoxic lethal toxin and edema toxin of B. anthracis.

13 NONCLINICAL TOXICOLOGY

13.1 Carcinogenesis, Mutagenesis and Impairment of Fertility

CYFENDUS has not been evaluated for carcinogenicity, mutagenic potential, or male infertility in animals. CYFENDUS administered to female rats had no effect on fertility [see Use in Specific Populations (8.1)].

13.2 Animal Toxicology and/or Pharmacology

Animal Pharmacology

Because it is not feasible or ethical to conduct controlled clinical trials with anthrax, the efficacy of CYFENDUS is based on animal studies with CYFENDUS and BioThrax. Pre-exposure prophylaxis studies conducted in animal models were used to derive protective antibody thresholds to bridge animal efficacy and human immunogenicity data and predict efficacy in humans.

Pivotal efficacy animal studies with BioThrax were conducted in rabbits and nonhuman primates (NHPs). Animals received two intramuscular vaccinations four weeks apart with serial dilutions of BioThrax and were subjected to lethal challenge on study day 70 with aerosolized B. anthracis spores at a target dose exceeding the 50% lethal dose by 200-fold. Serum samples were collected at various time points prior to challenge for immune response analysis via anthrax lethal toxin neutralizing antibody (TNA) assay. The relationship between pre-challenge serum TNA levels and survival was evaluated. Logistic regression analysis demonstrated that a 70% probability of survival was associated with a TNA NF50 (50% neutralization factor) level of 0.56 in rabbits and 0.29 in NHPs.

Efficacy studies for CYFENDUS were conducted in guinea pigs and cynomolgus macaques. Animals received two intramuscular vaccinations two weeks apart with various dilutions of CYFENDUS and were challenged with a lethal dose of aerosolized B. anthracis spores on Day 28 or 70. The studies demonstrated a strong correlation between pre-challenge serum TNA levels and survival.

The ability of CYFENDUS to increase survival after the cessation of the post-exposure antibacterial treatment, as compared with antibacterial treatment alone, was investigated in a guinea pig post-exposure prophylaxis study. In this study, guinea pigs were challenged with a lethal dose of aerosolized B. anthracis spores on Day 0 and treated with ciprofloxacin (7.5 mg/kg three times daily) for two weeks after the challenge. Various dilutions of the vaccine were administered on Days 1 and 8 after the challenge. Post-exposure vaccination increased animal survival in the 21-day period following cessation of antibacterial drugs, compared with antibacterial treatment alone, in a dose-dependent manner.

14 CLINICAL STUDIES

14.1 Post-Exposure Prophylaxis

The efficacy of CYFENDUS is based on studies of both CYFENDUS and BioThrax in animals [see Animal Toxicology and/or Pharmacology (13.2)].

Based on the animal model-derived TNA thresholds from studies of BioThrax, a multicenter, randomized, active-controlled, double-blind, parallel-group clinical study (Study 4; NCT03877926) was conducted to evaluate the immunogenicity and safety of a post-exposure administration schedule of two doses (0.5 mL) of CYFENDUS intramuscularly two weeks apart in adults ages 18 through 65 years. In the study, 3151 participants received at least one dose of CYFENDUS, and 533 participants received at least one dose (0.5 mL) of the comparator licensed anthrax vaccine, BioThrax. Participants were followed for immunogenicity up to Day 64 (7 weeks after last CYFENDUS vaccination, 5 weeks after last BioThrax vaccination) [see Adverse Reactions (6.1)].

The mean age of participants in the per protocol (PP) population receiving CYFENDUS (n=2543) was 39.4 years. Of these, 57.8% of participants were female, 78.1% were White, 17.0% were Black or African American, 1.7% were Multiracial, 1.6% were Asian, 0.5% were Other, 0.4% were American Indian or Alaskan Native, and 0.4% were Native Hawaiian or Pacific Islander. There were 13.8% Hispanic or Latino participants.

The primary immunogenicity objectives were to assess CYFENDUS vaccine-induced TNA 50% neutralization factor (NF50) response at Day 64 and noninferiority to BioThrax following two doses of CYFENDUS administered intramuscularly two weeks apart (Week 0 and 2) and three doses of BioThrax administered subcutaneously two weeks apart (Week 0, 2, and 4). The two co-primary immunogenicity endpoints and statistical evaluation criteria were:

- Percentage of CYFENDUS recipients achieving a threshold TNA NF50 value ≥0.56 at Day 64 (with the lower bound of the 2-sided 95% confidence interval [CI] for the proportion ≥40%) and,
- The percent difference between participants achieving a threshold TNA NF50 value ≥0.29 at Day 64 in those who received CYFENDUS and those who received BioThrax (with the lower bound of the 2-sided 95% CI for the difference being greater than -15%).

The TNA NF50 thresholds of 0.56 and 0.29 were based on the TNA NF50 values in rabbits and nonhuman primates, respectively, that were associated with 70% probability of survival in pre-exposure prophylaxis studies, in which animals were immunized with BioThrax and subsequently challenged with aerosolized B. anthracis spores [see Animal Toxicology and/or Pharmacology (13.2)].

Overall, 66.3% of CYFENDUS participants from the PP population achieved threshold TNA NF50 value ≥0.56 on Day 64 in the study; the lower bound of the 95% CI was 64.4% (Table 2).

Table 2. Percentage of Participants Achieving TNA NF50 Threshold in Clinical Study 4 at Day 64 After Administration of Two Doses of CYFENDUS (Per Protocol Population)
Day 64 | CYFENDUS
N= number of participants in PP population | 2543
Percent (95% CI) of participants meeting the TNA NF50 ≥0.56 threshold | 66.3 (64.4, 68.1)
CI = Confidence interval; NF50 = 50% neutralization factor; PP = Per protocol; TNA = Toxin neutralizing antibody.
CYFENDUS was considered to have achieved a protective level of immunity at Day 64 if the lower bound for the two-sided 95% CI for the percentage of participants with TNA NF50 values above the specified threshold of protection (≥0.56) was ≥40%.

The percent of participants with a threshold TNA NF50 of ≥0.29 at Day 64 was 86.6% in the CYFENDUS group compared with 61.4% in the BioThrax group, corresponding to a difference of 25.2%. The lower bound of the 2-sided 95% CI for the difference was 20.5%, thereby demonstrating noninferiority of CYFENDUS to BioThrax (Table 3).

Table 3. Noninferiority of CYFENDUS to BioThrax Based on Difference in Percentage of Participants Achieving TNA NF50 Threshold in Clinical Study 4 at Day 64 (Per Protocol Population)
 | CYFENDUS (N=2543); %; [95% CI] | BioThrax (N=430); %; [95% CI] | Difference (CYFENDUS-BioThrax) %; [95% CI]
Percent of Participants with TNA NF50 ≥0.29 | 86.6; [85.2, 87.9] | 61.4; [56.6, 66.0] | 25.2; [20.5, 30.1]
CI = Confidence interval; N = Number of participants in the study arm in the Per Protocol population;
% = Percent of participants achieving the target TNA NF50 threshold; NF50 = 50% neutralization factor; TNA = Toxin-neutralizing antibody
Noninferiority to BioThrax is based on the lower bound of the two-sided 95% CI for the difference in percentage (CYFENDUS – BioThrax) being above -15%.

14.2 Concomitant Administration with Ciprofloxacin or Doxycycline

A randomized, open-label, multicenter study (Study 3; NCT04067011) was conducted in males and females, age 18 to 45 years, to investigate the potential interactions of concomitant intramuscular administration of CYFENDUS with oral administration of ciprofloxacin or doxycycline. The potential effect of CYFENDUS vaccination on ciprofloxacin or doxycycline serum levels was assessed by evaluating steady-state pharmacokinetic profiles of ciprofloxacin or doxycycline before and after vaccination with a two-dose series of CYFENDUS.

Concomitant administration of 0.5 mL of CYFENDUS intramuscularly with oral ciprofloxacin or doxycycline in participants did not have a clinically relevant impact on the pharmacokinetics of ciprofloxacin and doxycycline, or the immunogenicity of CYFENDUS as measured by the TNA assay.

15 REFERENCES

1. Ryan MA, Smith TC, Sevick CJ, Honner WK, Loach RA, Moore CA, Erickson JD, 2008. Birth defects among infants born to women who received anthrax vaccine in pregnancy. Am J Epidemiol, 168:434-442.

16 HOW SUPPLIED/STORAGE AND HANDLING

16.1 How Supplied

CYFENDUS is supplied in multiple-dose vials containing ten 0.5 mL doses.

NDC 71665-001-01 (vial), 71665-001-02 (carton)

The vial stoppers are not made with natural rubber latex.

16.2 Storage and Handling

Store at 2°C to 8°C (36°F to 46°F).

Protect vials from light.

To avoid foaming DO NOT shake.

Do not freeze. Discard if product has been frozen.

Do not use CYFENDUS after the expiration date printed on the label.

- Once the stopper of the multiple-dose vial has been pierced, discard the vial within 28 days.
- Write the date of discard (28 days after the vial stopper was first pierced) on the vial and the carton in the designated area.
- Between uses, store the multiple-dose vial at 2°C to 8°C (36°F to 46°F).
- The date of discard should not exceed the manufacturer’s expiration date printed on the label.

17 PATIENT COUNSELING INFORMATION

Advise the patient to read the FDA-approved patient labeling (Patient Information).

Advise women of the potential risk to the fetus.

Inform patients of the benefits and risks of immunization with CYFENDUS.

Instruct patients to report any serious adverse reaction to their healthcare provider.

Manufactured by:

Emergent BioDefense Operations Lansing LLC
Lansing, MI USA 48906
License No. 1755

Distributed by:

Emergent Product Development Gaithersburg Inc.
Gaithersburg, MD USA 20879
License No. 2089

CYFENDUS®, BioThrax® and any and all Emergent BioSolutions Inc. brands, products, services and feature names, logos and slogans are trademarks or registered trademarks of Emergent BioSolutions Inc. or its subsidiaries in the United States or other countries.

Patient Information

CYFENDUS® (Anthrax Vaccine Adsorbed, Adjuvanted)

for intramuscular use

Please read this Patient Information summary carefully before you get this vaccine. This summary does not take the place of talking with your healthcare provider about CYFENDUS. If you have questions or would like more information, please talk with your healthcare provider.

What is CYFENDUS?

- CYFENDUS is a vaccine licensed by the FDA to protect against anthrax disease when given with recommended antibacterial drugs in persons 18 through 65 years of age after exposure to anthrax.
- CYFENDUS may not protect all vaccine recipients from anthrax disease.
- How well CYFENDUS works when given after exposure to anthrax has been studied only in animals. It has not been studied in humans because there are not enough people who get the disease naturally, and it is not ethical to expose people to anthrax on purpose to find out how well CYFENDUS works.
- The safety of CYFENDUS was studied in adults 18 through 65 years of age.

Who should not get CYFENDUS?

You should not get CYFENDUS if you have a history of severe allergic reaction to any ingredient of the vaccine, including aluminum hydroxide, benzethonium chloride, formaldehyde, or CPG 7909 or had a serious reaction after getting CYFENDUS or BioThrax® (Anthrax Vaccine Adsorbed) previously

What should I tell my healthcare provider before getting CYFENDUS?

- If you may be pregnant, plan to get pregnant soon, or are nursing a baby.
- About medicines that you take, including over-the-counter medicines and supplements.
- About immune problems you have, including steroid treatments and cancer treatments.

What if I discover I was pregnant at the time I got CYFENDUS?

- Inform your healthcare provider

How is CYFENDUS given?

CYFENDUS is given as an injection in your muscle.

After getting the first dose, you should come back for the second dose two weeks later. It is important that you get both doses.

You are being given CYFENDUS because you may have been exposed to anthrax. It is important that you also take antibacterial drugs as recommended by your healthcare provider.

What are the possible or reasonably likely side effects of CYFENDUS?

The most common side effects of CYFENDUS are:

- Pain/tenderness, warmth, hardness, itching, swelling, redness, and bruising at the injection site
- Problems moving the arm in which you received the vaccine
- Muscle aches
- Tiredness
- Headache
- Fever

Tell your healthcare provider about any side effects that concern you and ask about acceptable treatments for relief of side effects. There may be other side effects that are not listed here. Talk to your healthcare provider if you have questions or concerns about possible side effects.

You may report side effects to FDA by calling 1-800-822-7967 or to the website www.vaers.hhs.gov. You may also report side effects directly to Emergent BioSolutions at 1-800-768-2304 or at medicalinformation@ebsi.com.

What are the ingredients in CYFENDUS?

CYFENDUS does not contain live bacteria. CYFENDUS contains bacterial proteins that are not alive and do not cause anthrax disease. CYFENDUS also contains aluminum hydroxide and CPG 7909 as adjuvants (substances added to some vaccines to enhance the immune response of vaccinated individuals), and benzethonium chloride and formaldehyde as preservatives.

Distributed by:
Emergent Product Development Gaithersburg Inc.

Gaithersburg, MD USA 20879

License No. 2089

Issued: 11/2025

CYFENDUS DHCP Letter – 28-Day Discard Statement

11/2025

IMPORTANT PRESCRIBING INFORMATION

Subject: Important Labeling Update for CYFENDUS® (Anthrax Vaccine Adsorbed, Adjuvanted): 28-Day Discard After Vial Puncture Instructions

Dear Healthcare Provider:

The purpose of this letter is to inform you of an important update to the labeling of CYFENDUS® (Anthrax Vaccine Adsorbed, Adjuvanted), specifically regarding the storage and handling of the multiple-dose vial once it has been pierced.

Effective immediately, the following information has been added to the United States Prescribing Information (USPI), Section 2.2 Administration to state:
Once the stopper of the multiple-dose vial has been pierced, discard the vial within 28 days.

Additional information on the 28-day discard date has been included in Section 16.2 Storage and Handling, to state:

- Once the stopper of the multiple-dose vial has been pierced, discard the vial within 28 days.
- Between uses, store the multiple-dose vial at 2°C to 8°C (36°F to 46°F).
- The date of discard should not exceed the manufacturer’s expiration date printed on the label.

Healthcare Provider Action

To ensure proper storage and handling of CYFENDUS®, healthcare providers are instructed to:

- Ensure that the multiple-dose vial is stored at 2°C to 8°C (36°F to 46°F) between uses
- Discard the vial within 28 days of first puncture
- Ensure that the discard date does not exceed the expiration date printed on the vial
- Ensure all clinical staff are informed and trained on these instructions

Reporting Adverse Events

Report adverse events following CYFENDUS® administration to FDA by calling 1-800-822-7967 or to the website www.vaers.hhs.gov. You may also report side effects directly to Emergent BioSolutions at 1-800-768-2304 or at medicalinformation@ebsi.com.

If you require further guidance regarding the information contained in this letter, please contact medicalinformation@ebsi.com or call 1-888-483-9053.

This letter is not intended as a complete description of the benefits and risks related to the use of CYFENDUS®; please refer to the enclosed full prescribing information.

Sincerely,
Scott White, M.D.
Vice President, Head of Clinical Development
Interim Head of Global Patient Safety
Emergent BioSolutions

PRINCIPAL DISPLAY PANEL

NDC 71665-001-01

Anthrax Vaccine
Adsorbed,
Adjuvanted

CYFENDUS®

Contains
ten doses of 0.5 mL
for intramuscular use

Rx Only

U.S. License No. 2089

LBL040170-03

STRATEGIC NATIONAL STOCKPILE USE ONLY

Store at 2°C to 8°C (36°F to 46°F). DO NOT FREEZE.

Gently swirl or roll before use. Do not shake.

Discard after: ______/______/______

Dist. by Emergent Product Development
Gaithersburg, MD 20879 USA.

PRINCIPAL DISPLAY PANEL

NDC 71665-001-02

Anthrax Vaccine
Adsorbed,
Adjuvanted

CYFENDUS®
Distributed by:
Emergent Product Development
Gaithersburg Inc.
Gaithersburg, MD 20879 U.S.A.

U.S. License No. 2089
Rx Only